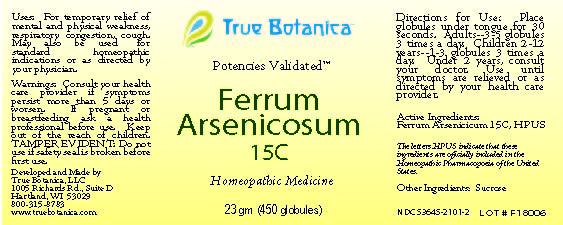 DRUG LABEL: Ferrum Arsenicosum
NDC: 53645-2101 | Form: GLOBULE
Manufacturer: True Botanica, LLC
Category: homeopathic | Type: HUMAN OTC DRUG LABEL
Date: 20230620

ACTIVE INGREDIENTS: FERROUS ARSENATE 15 [hp_C]/23 g
INACTIVE INGREDIENTS: SUCROSE

Ferrum Arsenicosum 15C

ACTIVE INGREDIENT

Ferrum Arsenicosum 15C, HPUS

The letters HPUS indicate that these ingredients are officially included in the Homeopathic Pharmacopoeia of the United States.

PURPOSE

For temporary relief of mental and physical weakness, respiratory congestion, cough. May also be used for standard homeopathic indications or as directed by your physician.

Use:

For temporary relief of mental and physical weakness, respiratory congestin, cough. May also be used for standard homeopathic indications or as directed by your physician.

Warnings:

Consult your health care provider if symptoms persist more than 5 days or worsen.

PREGNANCY OR BREAST FEEDING

If pregnant or breastfeeding ask a health professional before use.

Keep out of the reach of children.

DO NOT USE

TAMPER EVIDENT: Do not use if safety seal is broken before first use.

Directions for Use:

Place globules under tongue for 30 seconds. Adults~3-5 globules 3 times a day. Children 2-12 years ~ 1-3 globules 3 times a day. Under 2 years, consult your doctor. Use until symptoms are relieved or as directed by your health care provider.

Other Ingredients:

Sucrose

QUESTIONS

Developed and Made by

True Botanica, LLC

1005 Richards Rd., Suite D

Hartland, WI 53029

800-315-8783

www.truebotanica.com